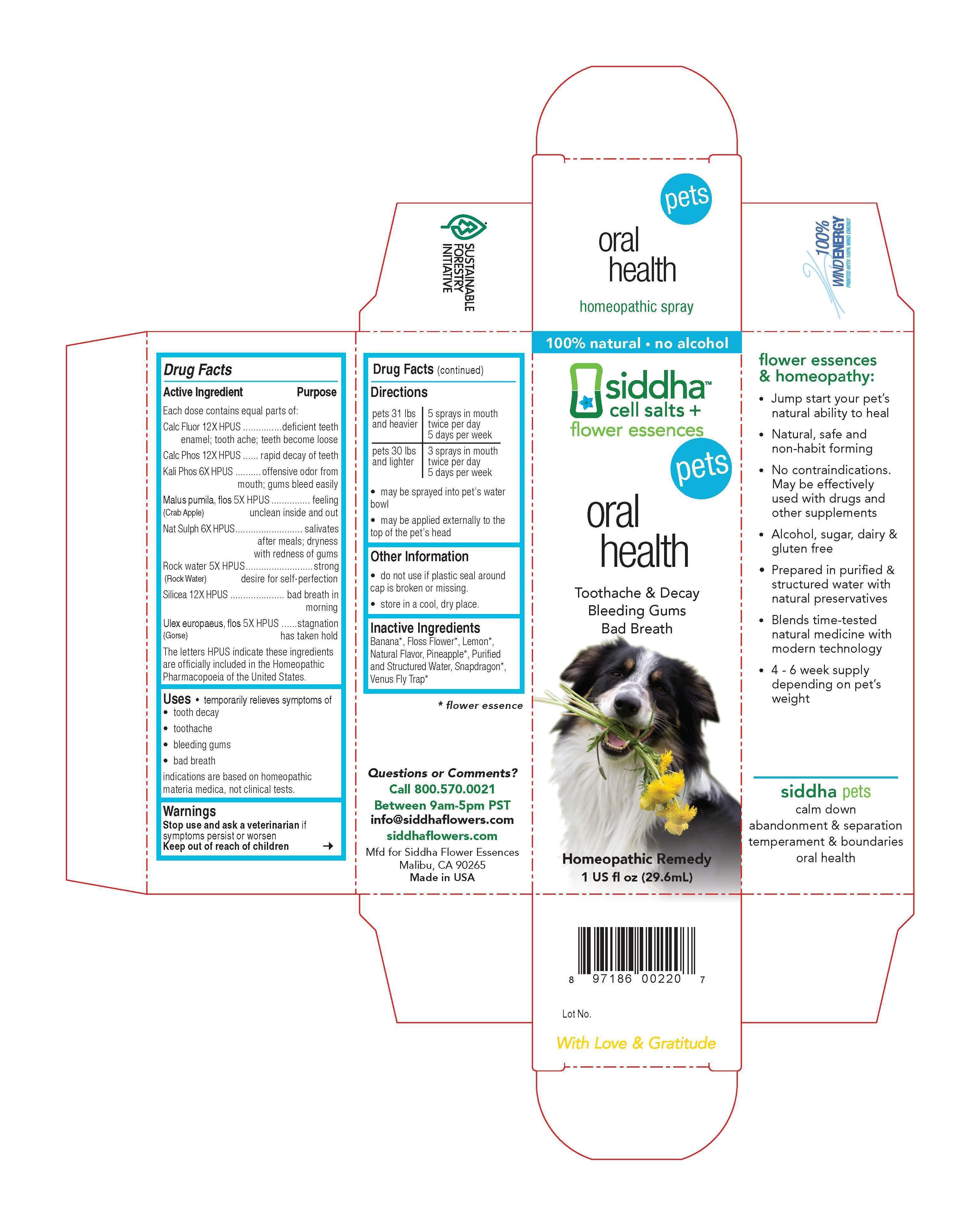 DRUG LABEL: oral health
NDC: 69779-023 | Form: SPRAY
Manufacturer: Siddha Flower Essences LLC
Category: homeopathic | Type: OTC ANIMAL DRUG LABEL
Date: 20150409

ACTIVE INGREDIENTS: CALCIUM FLUORIDE  12 [hp_X]/29.6 mL; TRIBASIC CALCIUM PHOSPHATE 12 [hp_X]/29.6 mL; POTASSIUM PHOSPHATE, DIBASIC 6 [hp_X]/29.6 mL; MALUS DOMESTICA FLOWER 5 [hp_X]/29.6 mL; SODIUM SULFATE 6 [hp_X]/29.6 mL; WATER 5 [hp_X]/29.6 mL; SILICON DIOXIDE 12 [hp_X]/29.6 mL; ULEX EUROPAEUS FLOWER 5 [hp_X]/29.6 mL
INACTIVE INGREDIENTS: MUSA X PARADISIACA FLOWER; LEMON; PINEAPPLE

Drug Facts

Active Ingredient

Each dose contains equal parts of:

Calc Fluor 12X HPUS
Calc Phos 12X HPUS
Kali Phos 6X HPUS
Malus pumila, flos (Crab Apple) 5X HPUS
Nat Sulph 6X HPUS
Rock Water (Rock Water) 5X HPUS
Silicea 12X HPUS
Ulex europaeus, flos (Gorse) 5X HPUS

Purpose

Each dose contains equal parts of:
Calc Fluor 12X HPUS.....................................deficient teeth enamel; tooth ache; teeth become loose
Calc Phos 12X HPUS....................................rapid decay of teeth
Kali Phos 6X HPUS......................................offensive oder from mouth; gums bleed easily
Malus pumila, flos (Crab Apple) 5X HPUS.......feeling unclean inside and out
Nat Sulph 6X HPUS......................................salivates after meals; dryness with redness of gums
Rock Water (Rock Water) 5X HPUS...............strong desire for self-perfection
Silicea 12X HPUS........................................bad breath in morning
Ulex europaeus, flos (Gorse) 5X HPUS..........stagnation has taken hold
The letters HPUS indicate these ingredients are officially included in the Homeopathic Pharmacopoeia of the United States.

Purpose

- temporarily relieves symptoms of
- tooth decay
- toothache
- bleeding gums
- bad breath

indications are based on homeopathic materia medica, not clinical tests.

Warnings

Stop use and ask a veterinarian if symptoms persist or worsen

Keep out of reach of children

Directions

pets 31 lbs and heavier | 5 sprays in mouth twice per day 5 days per week
pets 30 lbs and lighter | 3 sprays in mouth twice per day 5 days per week

- may be sprayed into pet's water bowl
- may be applied externally to the top of pet's head

Other Information

- do not use if plastic seal around cap is broken or missing.
- store in a cool, dry place.

Inactive Ingredients

Banana*, Floss Flower*, Lemon*, Natural Flavor, Pineapple*, Purified and Structured Water, Snapdragon*, Venus Fly Trap*

*flower essence

Questions or Comments?
Call 800.570.0021
Between 9am-5pm PST
info@siddhaflowers.com
siddhaflowers.com
Mfd for Siddha Flower Essences
Malibu, CA 90265
Made in USA

Side Panel

flower essences and homeopathy:

- Jump start your pet's natural ability to heal
- Natural, safe and non-habit forming
- No contraindications. May be effectively used with drugs and other supplements
- Alcohol, sugar, dairy and gluten free
- Prepared in purified and structured water with natural preservatives
- Blends time-tested natural medicine with modern technology
- 4 - 6 week supply depending on pet's weight

siddha pets
calm down
abandonment and separation
temperament and boundaries
oral health

Principal Display Panel

100% natural - no alcohol
siddha cell salts + flower essences
pets
oral health
Toothache and Decay
Bleeding Gums
Bad Breath
Homeopathic Remedy
1 US fl oz (29.6mL)